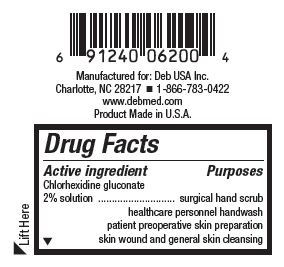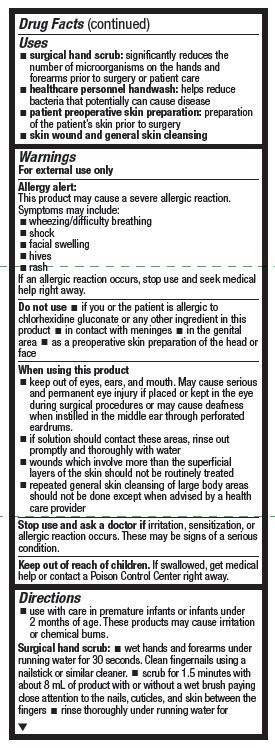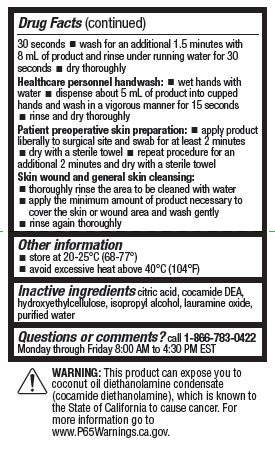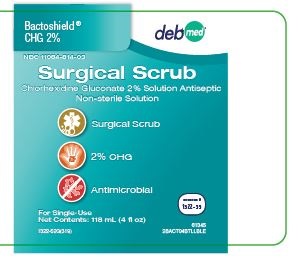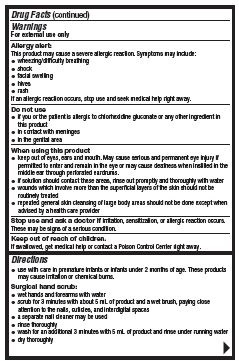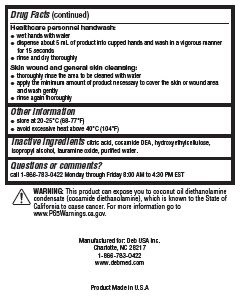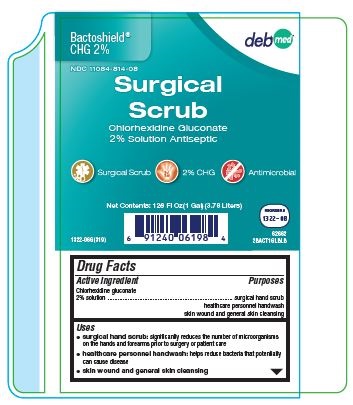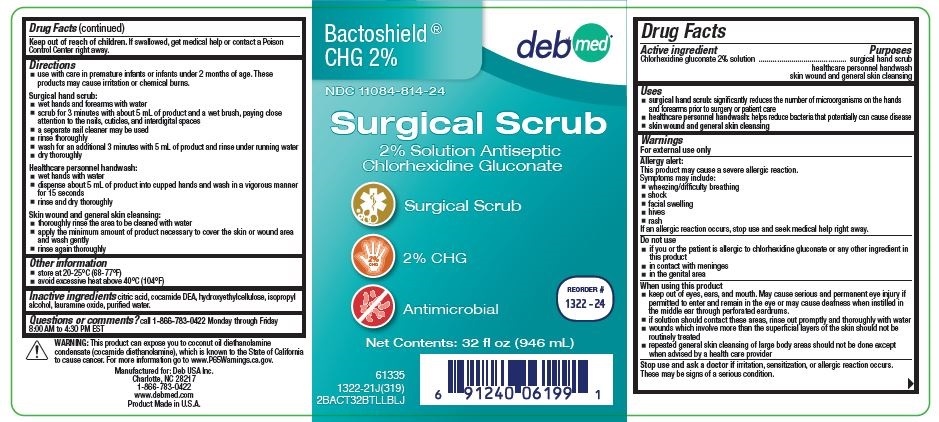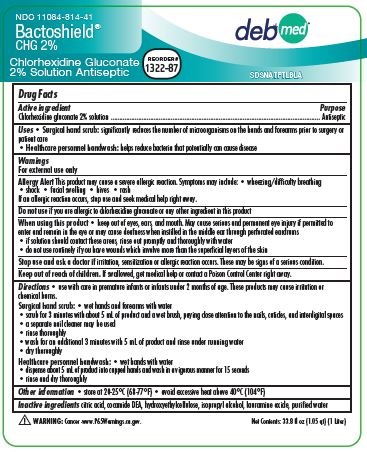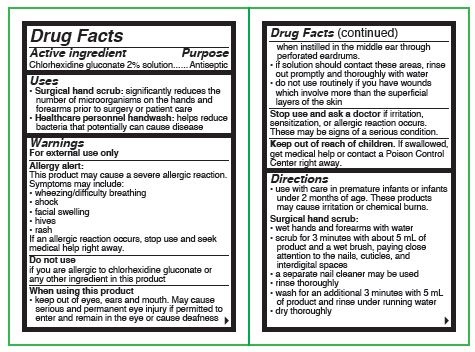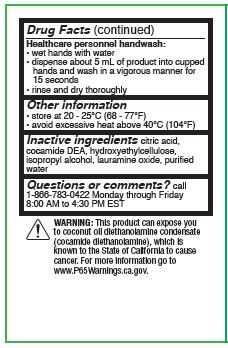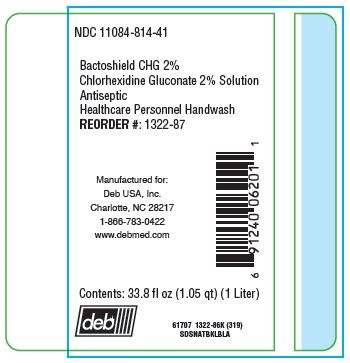 DRUG LABEL: Bactoshield CHG
NDC: 0116-1322 | Form: SOLUTION
Manufacturer: Xttrium Laboratories, Inc.
Category: otc | Type: HUMAN OTC DRUG LABEL
Date: 20191105

ACTIVE INGREDIENTS: CHLORHEXIDINE GLUCONATE 20 mg/1 mL
INACTIVE INGREDIENTS: CITRIC ACID MONOHYDRATE; COCO DIETHANOLAMIDE; HYDROXYETHYL CELLULOSE (100 MPA.S AT 2%); ISOPROPYL ALCOHOL; LAURAMINE OXIDE; WATER

Bactoshield® CHG 2%
Chlorhexidine Gluconate 2% Solution

Drug Facts

Active ingredient

chlorhexidine gluconate 2% solution

Purposes

surgical hand scrub
healthcare personnel handwash
patient preoperative skin preparation
skin wound and general skin cleansing

Uses

- surgical hand scrub: significantly reduces the number of microorganisms on the hands and forearms prior to surgery or patient care
- healthcare personnel handwash: helps reduce bacteria that potentially can cause disease
- patient preoperative skin preparation: preparation of the patient's skin prior to surgery
- skin wound and general skin cleansing

Warnings

For external use only

Allergy alert:

This product may cause a severe allergic reaction. Symptoms may include:

- wheezing/difficulty breathing
- shock
- facial swelling
- hives
- rash

If an allergic reaction occurs, stop use and seek medical help right away.

Do not use

- if you or the patient is allergic to chlorhexidine gluconate or any other ingredient in this product
- in contact with meninges
- in the genital area
- as a preoperative skin preparation of the head or face

When using this product

- keep out of eyes, ears and mouth. May cause serious and permanent eye injury if placed or kept in the eye during surgical procedures or may cause deafness when instilled in the middle ear through perforated eardrums
- if solution should contact these areas, rinse out promptly and thoroughly with water
- wounds which involve more than the superficial layers of the skin should not be routinely treated
- repeated general skin cleansing of large body areas should not be done except when advised by a health care provider

Stop use and ask a doctor if irritation, sensitization, or allergic reaction occurs. These may be signs of a serious condition.

Keep out of reach of children. If swallowed, get medical help or contact a Poison Control Center right away.

Directions

- use with care in premature infants or infants under 2 months of age. These products may cause irritation or chemical burns.

Surgical hand scrub:

- wet hands and forearms under running water for 30 seconds. Clean fingernails using a nailstick or similar cleaner.
- scrub for 1.5 minutes with about 8 mL of product with or without a wet brush paying close attention to the nails, cuticles, and skin between the fingers
- rinse thoroughly under the running water for 30 seconds
- wash for an additional 1.5 minutes with 8 mL of product and rinse under running water for 30 seconds
- dry thoroughly

Healthcare personnel handwash:

- wet hands with water
- dispense about 5 mL of product into cupped hands and wash in a vigorous manner for 15 seconds
- rinse and dry thoroughly

Patient preoperative skin preparation:

- apply product liberally to surgical site and swab for at least 2 minutes
- dry with a sterile towel
- repeat procedure for an additional 2 minutes and dry with a sterile towel

Skin wound and general skin cleansing:

- thoroughly rinse the area to e cleaned with water
- apply the minimum amount of product necessary to cover the skin or wound area and wash gently
- rinse again thoroughly

Other information

- store at 20 - 25°C (68 - 77°F)
- avoid excessive heat above 40°C (104°F)

Inactive ingredients

citric acid, cocamide DEA, hydroxyethylcellulose, isopropyl alcohol, lauramine oxide, purified water

Questions or comments?

Call 1-800-548-4873 Monday through Friday 8:00 AM to 4:30 PM CST

OTHER SAFETY INFORMATION

WARNING: This product can expose you to coconut oil diethanolamine condensate (cocamide diethanolamine), which is known to the State of California to cause. For more information go to www.P65Warnings.ca.gov

RECENT MAJOR CHANGES

Dosage and Administration

PACKAGE LABEL

Bactoshield ® CHG 2%

NDC 11084-814-03

Surgical Scrub

Chlorhexidine Gluconate 2% Solution Antiseptic

Non-sterile Solution

Surgical Scrub

2% CHG

Antimicrobial

For Single-Use

Net Contents: 118 mL (4 fl oz)

1322-52G(319)

REORDER #1322-39

61345

2BACT04BTLLBLE

Bactoshield® CHG 2%

NDC 11084-814-24

Surgical Scrub

2% Solution Antiseptic

Chlorhexidine Gluconate

Surgical Scrub

2% CHG

Antimicrobial

Net Contents: 32 fl oz (946 mL)

REORDER #1322-24

61335

1322-21J(319)

2BACT32BTLLBLJ

Bactoshield ® CHG 2%

NDC 11084-814-08

Surgical Scrub

Chlorhexidine Gluconate 2% Solution Antiseptic

Surgical Scrub

2% CHG

Antimicrobial

Net Contents: 128 fl oz (1Gal)(3.78 Liters)

1322-06G(319)

REORDER #1322-08

62662

2BACT1GLBLB

NDC 11084-814-41

Bactoshield CHG 2%

Chlorhexidine Gluconate 2% Solution

Antiseptic

Healthcare Personnel Handwash

REORDER #: 1322-87

Manufactured for:

Deb USA, Inc.

Charlotte, NC 28217

1-866-783-0422

www.debmed.com

Contents: 33.8 fl oz (1.05 qt) (1 Liter)

61707

1322-86K (319)

SDSNATBKLBLA

NDC 11084-814-41

SDSNATFTLBLA